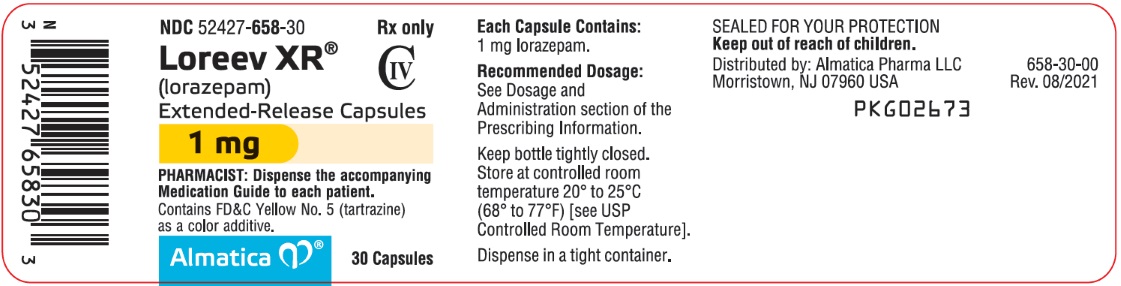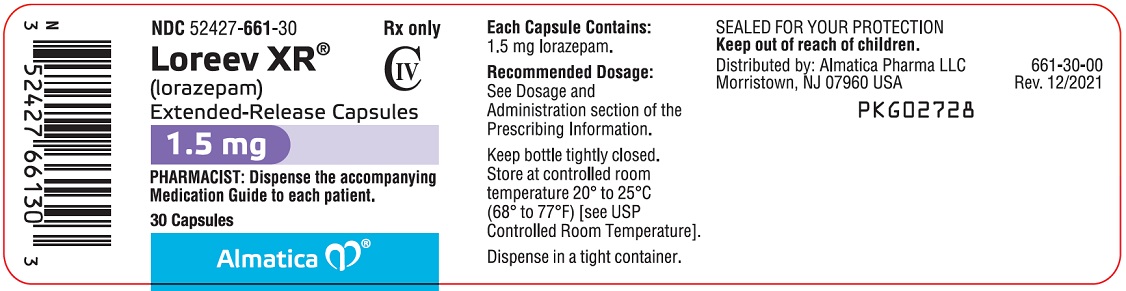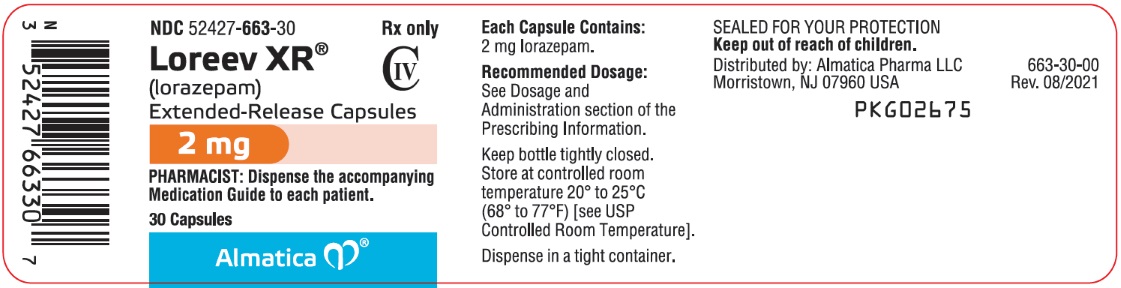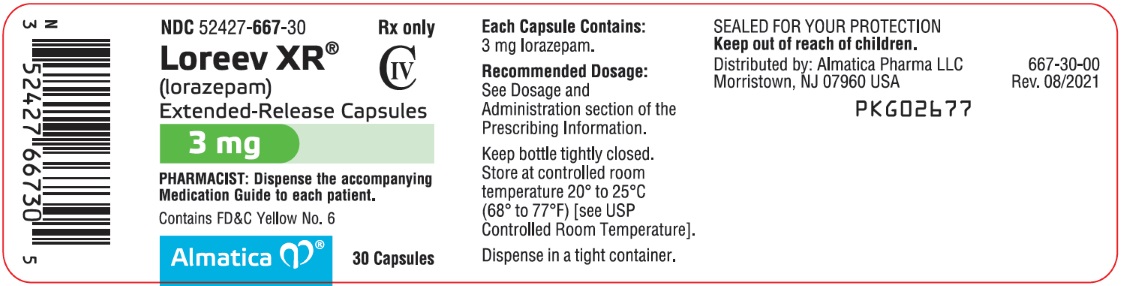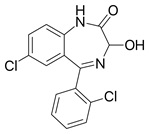 DRUG LABEL: LOREEV XR
NDC: 52427-658 | Form: CAPSULE, EXTENDED RELEASE
Manufacturer: Almatica Pharma LLC
Category: prescription | Type: HUMAN PRESCRIPTION DRUG LABEL
Date: 20251008
DEA Schedule: CIV

ACTIVE INGREDIENTS: LORAZEPAM 1 mg/1 1
INACTIVE INGREDIENTS: POLY(METHYL ACRYLATE-CO-METHYL METHACRYLATE-CO-METHACRYLIC ACID 7:3:1; 280000 MW); SILICON DIOXIDE; STARCH, CORN; GELATIN, UNSPECIFIED; GLYCERYL MONOSTEARATE; HYPROMELLOSE, UNSPECIFIED; LACTOSE MONOHYDRATE; MICROCRYSTALLINE CELLULOSE; POLYSORBATE 80; TALC; TITANIUM DIOXIDE; TRIETHYL CITRATE; FD&C YELLOW NO. 5

HIGHLIGHTS OF PRESCRIBING INFORMATION

These highlights do not include all the information needed to use LOREEV XR safely and effectively. See full prescribing information for LOREEV XR.
LOREEV XR (lorazepam) extended-release capsules, for oral use, CIV
Initial U.S. Approval: 1977

RECENT MAJOR CHANGES

Warnings and Precautions (5.8) | 1/2023

WARNING: RISKS FROM CONCOMITANT USE WITH OPIOIDS; ABUSE, MISUSE, AND ADDICTION; and DEPENDENCE AND WITHDRAWAL REACTIONS

See full prescribing information for complete boxed warning.

- Concomitant use of benzodiazepines and opioids may result in profound sedation, respiratory depression, coma, and death. Reserve concomitant prescribing of these drugs for use in patients for whom alternative treatment options are inadequate. Limit dosages and durations to the minimum required. Follow patients for signs and symptoms of respiratory depression and sedation (5.1, 7)
- The use of benzodiazepines, including LOREEV XR, exposes users to risks of abuse, misuse, and addiction, which can lead to overdose or death. Before prescribing LOREEV XR and throughout treatment, assess each patient’s risk for abuse, misuse, and addiction (5.2)
- Abrupt discontinuation or rapid dosage reduction of LOREEV XR after continued use may precipitate acute withdrawal reactions, which can be life-threatening. To reduce the risk of withdrawal reactions, use a gradual taper to discontinue LOREEV XR or reduce the dosage (2.4, 5.3)

1 INDICATIONS AND USAGE

LOREEV XR is a benzodiazepine indicated for the treatment of anxiety disorders in adults who are receiving stable, evenly divided, three times daily dosing with lorazepam tablets (1)

2 DOSAGE AND ADMINISTRATION

- Recommended dosage of LOREEV XR is equal to the total daily dose of lorazepam tablets (at the previous three times daily dosage) (2.1)
- Administer LOREEV XR orally once daily in the morning (2.2)
- Capsules may be swallowed whole or opened and the entire contents sprinkled onto applesauce. Do not crush or chew (2.2)
- For dosage adjustments, discontinue LOREEV XR and switch to lorazepam tablets to adjust dosage (2.3)

3 DOSAGE FORMS AND STRENGTHS

Extended-release capsules: 1 mg, 1.5 mg, 2 mg, and 3 mg (3)

4 CONTRAINDICATIONS

- Hypersensitivity to benzodiazepines or any ingredients in LOREEV XR (4)
- Acute narrow-angle glaucoma (4)

5 WARNINGS AND PRECAUTIONS

- CNS Depression: May cause CNS depression. Caution patients receiving LOREEV XR against operating machinery or driving a motor vehicle as well to avoid the concomitant use of alcohol and other CNS depressant drugs during treatment (5.4, 7)
- Patients with Depression or Psychosis: Use with caution in patients with signs or symptoms of depression. Prescribe the least number of capsules feasible to avoid intentional overdosage (5.5)
- Allergic Reactions to FD&C Yellow No. 5 (Tartrazine): Contains FD&C Yellow No. 5 (tartrazine) which may cause allergic type reactions (including bronchial asthma) in certain susceptible persons (5.7)
- Neonatal Sedation and Withdrawal Syndrome: LOREEV XR use during pregnancy can result in neonatal sedation and/or withdrawal (5.8, 8.1)

6 ADVERSE REACTIONS

Most frequent adverse reactions: sedation, dizziness, weakness, unsteadiness (6)

To report SUSPECTED ADVERSE REACTIONS, contact Almatica Pharma LLC at 1-877-447-7979 or FDA at 1-800-FDA-1088 or www.fda.gov/medwatch.

7 DRUG INTERACTIONS

- Use with Opioids: Increase the risk of respiratory depression (7)
- CNS depressants: Additive CNS depressant effects (7)
- Alcohol: Avoid use. Increases the release rate of LOREEV XR (7)
- UGT Inhibitors: Avoid initiation of UGT inhibitors. Dose reduction requires switching to lorazepam tablets for dose adjustment (7)

8 USE IN SPECIFIC POPULATIONS

- Lactation: Breastfeeding not recommended (8.2)

FULL PRESCRIBING INFORMATION

WARNING: RISKS FROM CONCOMITANT USE WITH OPIOIDS; ABUSE, MISUSE, AND ADDICTION; and DEPENDENCE AND WITHDRAWAL REACTIONS

- Concomitant use of benzodiazepines and opioids may result in profound sedation, respiratory depression, coma, and death. Reserve concomitant prescribing of these drugs for patients for whom alternative treatment options are inadequate. Limit dosages and durations to the minimum required. Follow patients for signs and symptoms of respiratory depression and sedation [see Warnings and Precautions (5.1), Drug Interactions (7)].
- The use of benzodiazepines, including LOREEV XR, exposes users to risks of abuse, misuse, and addiction, which can lead to overdose or death. Abuse and misuse of benzodiazepines commonly involve concomitant use of other medications, alcohol, and/or illicit substances, which is associated with an increased frequency of serious adverse outcomes. Before prescribing LOREEV XR and throughout treatment, assess each patient’s risk for abuse, misuse, and addiction [see Warnings and Precautions (5.2)].
- The continued use of benzodiazepines, including LOREEV XR, may lead to clinically significant physical dependence. The risks of dependence and withdrawal increase with longer treatment duration and higher daily dose. Abrupt discontinuation or rapid dosage reduction of LOREEV XR after continued use may precipitate acute withdrawal reactions, which can be life-threatening. To reduce the risk of withdrawal reactions, use a gradual taper to discontinue LOREEV XR or reduce the dosage [see Dosage and Administration (2.4), Warnings and Precautions (5.3)].

1 INDICATIONS AND USAGE

LOREEV XR is indicated for the treatment of anxiety disorders in adults who are receiving stable, evenly divided, three times daily dosing with lorazepam tablets.

2 DOSAGE AND ADMINISTRATION

2.1 Recommended Dosage

Initiate LOREEV XR in patients who are being treated with lorazepam tablets, administered three times daily in evenly divided doses (refer to the Prescribing Information of lorazepam tablets for the recommended dosage of lorazepam tablets).

Discontinue lorazepam tablets and administer the first dose of LOREEV XR in the morning the day after the final dose of lorazepam tablets.

The recommended once daily dosage of LOREEV XR is equal to the total daily dose of lorazepam tablets. For example, the recommended dosage for patients who have been receiving lorazepam tablets at a dosage of 1 mg three times daily is LOREEV XR 3 mg once daily in the morning.

The effectiveness of LOREEV XR use for more than 4 months has not been assessed in clinical studies. Healthcare providers should periodically re-evaluate longer term use of LOREEV XR.

2.2 Administration Information

Administer LOREEV XR orally once daily, in the morning, with or without food. Do not crush or chew LOREEV XR.

Swallow LOREEV XR capsules whole or open the capsule and sprinkle the entire contents over a tablespoon of applesauce, followed by drinking water. Consume all the sprinkled LOREEV XR in its entirety, (without chewing) within 2 hours; do not store for future use.

2.3 Dosage Increase for Inadequate Clinical Response

If the clinical response to LOREEV XR is inadequate and a dosage increase in needed, discontinue LOREEV XR and switch to lorazepam tablets to increase the dosage. If an adequate clinical response is achieved with a stable, evenly divided three times daily dosage of lorazepam tablets, resume LOREEV XR once daily dosing with the total daily dose of lorazepam tablets [see Dosage and Administration (2.1)].

2.4 Discontinuation or Dosage Reduction of LOREEV XR

To reduce the risk of withdrawal reactions, use a gradual taper to discontinue LOREEV XR or reduce the dosage. If a patient develops withdrawal reactions, consider pausing the taper or increasing the dosage to the previous tapered dosage level. Subsequently decrease the dosage more slowly [see Warnings and Precautions (5.3), Drug Abuse and Dependence (9.3)].

2.5 Concomitant Use with UDP-glucuronosyltransferase (UGT) Inhibitors

If an UGT inhibitor is initiated during treatment with LOREEV XR, discontinue LOREEV XR and switch to lorazepam tablets to reduce the dosage [see Dosage and Administration (2.4), Drug Interactions (7)].

3 DOSAGE FORMS AND STRENGTHS

LOREEV XR (lorazepam) extended-release capsules are available as:

1 mg: Hard gelatin capsules with an opaque white body, yellow cap and grey printing ink; "ALM" is printed axially on the yellow cap and "658" is printed axially on the opaque white body

1.5 mg: Hard gelatin capsules with an opaque white body, purple cap and black printing ink; "ALM" is printed axially on the purple cap and "661" is printed axially on the opaque white body

2 mg: Hard gelatin capsules with an opaque white body, orange cap and grey printing ink; "ALM" is printed axially on the orange cap and "663" is printed axially on the opaque white body

3 mg: Hard gelatin capsules with an opaque white body, yellowish-green cap and grey printing ink; "ALM" is printed axially on the yellowish-green cap and "667" is printed axially on the opaque white body

4 CONTRAINDICATIONS

LOREEV XR is contraindicated in patients with:

- hypersensitivity to benzodiazepines or to any of the ingredients in LOREEV XR [see Warnings and Precautions (5.7)].
- acute narrow-angle glaucoma

5 WARNINGS AND PRECAUTIONS

5.1 Risks from Concomitant Use with Opioids

Concomitant use of benzodiazepines, including LOREEV XR, and opioids may result in profound sedation, respiratory depression, coma, and death. Because of these risks, reserve concomitant prescribing of these drugs in patients for whom alternative treatment options are inadequate.

Observational studies have demonstrated that concomitant use of opioid analgesics and benzodiazepines increases the risk of drug-related mortality compared to use of opioids alone. If a decision is made to prescribe LOREEV XR concomitantly with opioids, prescribe the lowest effective dosages and minimum durations of concomitant use, and follow patients closely for signs and symptoms of respiratory depression and sedation. In patients already receiving an opioid analgesic, prescribe a lower initial dose of LOREEV XR than indicated in the absence of an opioid and titrate based on clinical response. If an opioid is initiated in a patient already taking LOREEV XR, prescribe a lower initial dose of the opioid and titrate based upon clinical response.

Advise both patients and caregivers about the risks of respiratory depression and sedation when LOREEV XR is used with opioids. Advise patients not to drive or operate heavy machinery until the effects of concomitant use with the opioid have been determined [see Drug Interactions (7)].

5.2 Abuse, Misuse, and Addiction

The use of benzodiazepines, including LOREEV XR, exposes users to the risks of abuse, misuse, and addiction, which can lead to overdose or death. Abuse and misuse of benzodiazepines often (but not always) involve the use of doses greater than the maximum recommended dosage and commonly involve concomitant use of other medications, alcohol, and/or illicit substances, which is associated with an increased frequency of serious adverse outcomes, including respiratory depression, overdose, or death [see Drug Abuse and Dependence (9.2)].

Before prescribing LOREEV XR and throughout treatment, assess each patient’s risk for abuse, misuse, and addiction (e.g., using a standardized screening tool). Use of LOREEV XR, particularly in patients at elevated risk, necessitates counseling about the risks and proper use of LOREEV XR along with monitoring for signs and symptoms of abuse, misuse, and addiction. Prescribe the lowest effective dosage; avoid or minimize concomitant use of CNS depressants and other substances associated with abuse, misuse, and addiction (e.g., opioid analgesics, stimulants); and advise patients on the proper disposal of unused drug. If a substance use disorder is suspected, evaluate the patient and institute (or refer them for) early treatment, as appropriate.

5.3 Dependence and Withdrawal Reactions

To reduce the risk of withdrawal reactions, use a gradual taper to discontinue LOREEV XR or reduce the dosage (a patient-specific plan should be used to taper the dose) [see Dosage and Administration (2.4)].

Patients at an increased risk of withdrawal adverse reactions after benzodiazepine discontinuation or rapid dosage reduction include those who take higher dosages, and those who have had longer durations of use.

Acute Withdrawal Reactions

The continued use of benzodiazepines, including LOREEV XR, may lead to clinically significant physical dependence. Abrupt discontinuation or rapid dosage reduction of LOREEV XR after continued use, or administration of flumazenil (a benzodiazepine antagonist) may precipitate acute withdrawal reactions, which can be life-threatening (e.g., seizures) [see Drug Abuse and Dependence (9.3)].

Protracted Withdrawal Syndrome

In some cases, benzodiazepine users have developed a protracted withdrawal syndrome with withdrawal symptoms lasting weeks to more than 12 months [see Drug Abuse and Dependence (9.3)].

5.4 Central Nervous System (CNS) Depression

Benzodiazepines, including LOREEV XR, may produce CNS depression. Caution patients receiving LOREEV XR against engaging in hazardous occupations or activities requiring complete mental alertness such as operating machinery or driving a motor vehicle.

Use of benzodiazepines, including LOREEV XR, both used alone and in combination with other CNS depressants, may lead to potentially fatal respiratory depression. Alcohol should be avoided and other CNS depressant drugs used with caution during treatment with LOREEV XR [see Drug Interactions (7)].

5.5 Patients with Depression or Psychosis

LOREEV XR is not recommended for use in patients with a primary depressive disorder or psychosis. Pre-existing depression may emerge or worsen during use of benzodiazepines, including LOREEV XR.

In patients with depression, a possibility for suicide should be borne in mind. Consequently, appropriate precautions (e.g., limiting the total prescription size and increased monitoring for suicidal ideation) should be considered in patients with depression. LOREEV XR should not be used in such patients without adequate antidepressant therapy.

5.6 Risk of Paradoxical Reactions

Paradoxical reactions (agitation, irritability, impulsivity, violent behavior, confusion, restlessness, excitement, and talkativeness) have been reported during benzodiazepine use [see Adverse Reactions (6)]. Such reactions may be more likely to occur in the elderly [see Adverse Reactions (8.5)]. Discontinue LOREEV XR if the patient experiences these reactions.

5.7 Allergic Reactions to FD&C Yellow No. 5 (Tartrazine)

LOREEV XR 1 mg capsules contain FD&C Yellow No. 5 (tartrazine), which may cause allergic-type reactions (including bronchial asthma) in certain susceptible persons. Although the overall incidence of FD&C Yellow No. 5 (tartrazine) sensitivity in the general population is low, it is frequently seen in patients who also have aspirin hypersensitivity [see Contraindications (4)].

5.8 Neonatal Sedation and Withdrawal Syndrome

Use of LOREEV XR late in pregnancy can result in sedation (respiratory depression, lethargy, hypotonia) and/or withdrawal symptoms (hyperreflexia, irritability, restlessness, tremors, inconsolable crying, and feeding difficulties) in the neonate [see Use in Specific Populations (8.1)]. Monitor neonates exposed to LOREEV XR during pregnancy or labor for signs of sedation and monitor neonates exposed to LOREEV XR during pregnancy for signs of withdrawal; manage these neonates accordingly.

5.9 Risk in Patients with Impaired Respiratory Function

In patients with impaired respiratory function, respiratory depression and apnea have been reported with benzodiazepines. Closely monitor patients with impaired respiratory function. If signs and symptoms of respiratory depression or apnea occur, consider discontinuing LOREEV XR.

5.10 Laboratory Tests

Leukopenia and elevations of LDH have developed in patients receiving lorazepam tablets [see Adverse Reactions (6)]. Periodic blood counts and liver function tests are recommended for patients on long-term therapy.

6 ADVERSE REACTIONS

The following serious adverse reactions are described elsewhere in the labeling:

- Risks from Concomitant Use with Opioids [see Warnings and Precautions (5.1)]
- Abuse, Misuse, and Addiction [see Warnings and Precautions (5.2)]
- Dependence and Withdrawal Reactions [see Warnings and Precautions (5.3)]
- Central Nervous System (CNS) Depression [see Warnings and Precautions (5.4)]
- Patients with Depression or Psychosis [see Warnings and Precautions (5.5)]
- Allergic Reactions to FD&C Yellow No. 5 (Tartrazine) [see Warnings and Precautions (5.7)]
- Neonatal Sedation and Withdrawal Syndrome [see Warnings and Precautions (5.8)]
- Risk in Patients with Impaired Respiratory Function [see Warnings and Precautions (5.9)]

The safety of LOREEV XR in adults is based on studies with lorazepam tablets. The following adverse reactions associated with the use of lorazepam tablets were identified in clinical studies or postmarketing reports. Because some of these reactions were reported voluntarily from a population of uncertain size, it is not always possible to reliably estimate their frequency or establish a causal relationship to drug exposure.

In a sample of approximately 3,500 patients treated for anxiety, the most frequent adverse reactions to lorazepam tablets were sedation (15.9%), dizziness (6.9%), weakness (4.2%), and unsteadiness (3.4%). The incidence of sedation and unsteadiness increased with age.

The following reported adverse reactions are categorized by System Organ Class (SOC):

Blood and Lymphatic System Disorders: agranulocytosis, leukopenia, pancytopenia, thrombocytopenia

Endocrine Disorders: syndrome of inappropriate antidiuretic hormone (SIADH)

Eye Disorder: eye function/visual disturbance (including diplopia and blurred vision)

Gastrointestinal Disorder: constipation, gastrointestinal symptoms including nausea

General Disorders and Administration Site Conditions: asthenia, fatigue, hypothermia

Hepatobiliary Disorders: jaundice

Immune System Disorders: anaphylactoid reactions, hypersensitivity reactions

Investigations: increase in bilirubin, increase in liver transaminases (including elevated LDH), increase in alkaline phosphatase

Metabolism and Nutrition Disorders: change in appetite, hyponatremia

Nervous System Disorders: ataxia, autonomic manifestations, coma, convulsions/seizures, drowsiness, dysarthria/slurred speech, extrapyramidal symptoms, headache, tremor, vertigo, memory impairment

Psychiatric Disorders: amnesia, change in libido, confusion, decreased orgasm, depression, disinhibition, disorientation, euphoria, suicidal ideation/attempt, unmasking of depression

Reproductive System and Breast Disorders: impotence

Respiratory Thoracic and Mediastinal Disorders: apnea, respiratory depression, worsening of obstructive pulmonary disease, worsening of sleep apnea

Skin and Subcutaneous Tissue Disorder: allergic skin reactions, alopecia, dermatological symptoms

Paradoxical reactions, including anxiety, excitation, agitation, hostility, aggression, rage, sleep disturbances/insomnia, sexual arousal, and hallucinations may occur.

Small decreases in blood pressure and hypotension have been reported with immediate-release lorazepam.

Many adverse reactions to benzodiazepines, including CNS effects and respiratory depression, are dose dependent, with more severe effects occurring with high doses.

7 DRUG INTERACTIONS

Table 1 presents clinically significant interactions with LOREEV XR.

Table 1: Clinically Significant Drug Interactions with LOREEV XR.
Opioids
Clinical Impact | The concomitant use of benzodiazepines and opioids increases the risk of respiratory depression because of actions at different receptor sites in the CNS that control respiration. Benzodiazepines interact at gamma-aminobutyric acid (GABAA) sites and opioids interact primarily at mu receptors. When benzodiazepines and opioids are combined, the potential for benzodiazepines to significantly worsen opioid-related respiratory depression exists [see Warnings and Precautions (5.1)].
Intervention | Limit dosage and duration of concomitant use of LOREEV XR and opioids, and monitor patients closely for respiratory depression and sedation.
Alcohol
Clinical Impact | Based on an in vitro study, alcohol increases the release rate of LOREEV XR [see Clinical Pharmacology (12.3)].
Intervention | Avoid concomitant use of alcohol during treatment with LOREEV XR [see Warnings and Precautions (5.4)].
CNS-Depressants
Clinical Impact | Benzodiazepines, including LOREEV XR, increase CNS-depressant effects when administered with other CNS depressants. Concomitant use of clozapine and LOREEV XR may produce marked sedation, excessive salivation, hypotension, ataxia, delirium, and respiratory arrest.
Intervention | Avoid co-administration of alcohol with LOREEV XR. Use caution if LOREEV XR is co-administered with other CNS-depressants [see Warnings and Precautions (5.4)].
Inhibitors of UGT
Clinical Impact | Concomitant use of LOREEV XR with UGT inhibitors may increase lorazepam exposure [see Clinical Pharmacology (12.3)], which may increase the risk of adverse reactions.
Intervention | Avoid initiating an UGT inhibitor during treatment with LOREEV XR. If an UGT inhibitor is initiated, discontinue LOREEV XR and switch to lorazepam tablets [see Dosage and Administration (2.5)].

8 USE IN SPECIFIC POPULATIONS

8.1 Pregnancy

Pregnancy Exposure Registry

There is a pregnancy exposure registry that monitors pregnancy outcomes in women exposed to LOREEV XR during pregnancy. Health care providers are encouraged to register patients by calling the National Pregnancy Registry for Psychiatric Medications at 1-866-961-2388 or by visiting online at https://womensmentalhealth.org/pregnancyregistry.

Risk Summary

Neonates born to mothers using benzodiazepines late in pregnancy have been reported to experience symptoms of sedation and/or neonatal withdrawal [see Warnings and Precautions (5.8), Clinical Considerations]. Available data from published observational studies of pregnant women exposed to benzodiazepines do not report a clear association with benzodiazepines and major birth defects (see Data). In animal studies, administration of lorazepam during the organogenesis period of pregnancy resulted in increased incidences of fetal malformations at doses greater than those used clinically. Data for benzodiazepines suggest the possibility of increased neuronal cell death and long-term effects on neurobehavioral function based on findings in animals following prenatal or early postnatal exposure at clinically relevant doses (see Data).

The background risk of major birth defects and miscarriage for the indicated population is unknown. All pregnancies have a background risk of birth defect, loss, or other adverse outcomes. In the U.S. general population, the estimated background risk of major birth defects and miscarriage in clinically recognized pregnancies is 2% to 4% and 15% to 20%, respectively.

Clinical Considerations

Fetal/Neonatal Adverse Reactions

Benzodiazepines cross the placenta and may produce respiratory depression, hypotonia and sedation in neonates. Monitor neonates exposed to LOREEV XR during pregnancy or labor for signs of sedation, respiratory depression, hypotonia, and feeding problems. Monitor neonates exposed to LOREEV XR during pregnancy for signs of withdrawal. Manage these neonates accordingly [see Warnings and Precautions (5.8)].

Data

Human Data

Published data from observational studies on the use of benzodiazepines during pregnancy do not report a clear association with benzodiazepines and major birth defects. Although early studies reported an increased risk of congenital malformations with diazepam and chlordiazepoxide, there was no consistent pattern noted. In addition, the majority of more recent case-control and cohort studies of benzodiazepine use during pregnancy, which were adjusted for confounding exposures to alcohol, tobacco and other medications, have not confirmed these findings.

Animal Data

Reproductive studies in animals were performed in mice, rats, and two strains of rabbits. A low incidence of malformations (reduction of tarsals, tibia, metatarsals, mal-rotated limbs, gastroschisis, malformed skull, and microphthalmia) were seen in drug-treated rabbits without relationship to dosage. Although all of these anomalies were not present in the concurrent control group, they have been reported to occur randomly in historical controls. At doses of 40 mg/kg and higher there was evidence of fetal resorption and increased fetal loss in rabbits which was not seen at lower doses.

In published animal studies, administration of benzodiazepines or other drugs that enhance GABAergic inhibition to neonatal rats has been reported to result in widespread apoptotic neurodegeneration in the developing brain. The window of vulnerability to these changes in rats (postnatal days 0-14) includes a period of brain development that takes place during the third trimester of pregnancy in humans.

8.2 Lactation

Risk Summary

Lorazepam is present in breastmilk. There are reports of sedation, poor feeding and poor weight gain in infants exposed to benzodiazepines through breast milk. The effects of lorazepam on milk production are unknown.

Because of the potential for serious adverse reactions, including sedation and withdrawal symptoms in breastfed infants, advise patients that breastfeeding is not recommended during treatment with LOREEV XR.

8.4 Pediatric Use

The safety and effectiveness of LOREEV XR has not been established in pediatric patients.

8.5 Geriatric Use

Clinical studies of lorazepam tablets were not adequate to determine whether patients age 65 years and older responded differently than younger patients; however, the incidence of sedation and unsteadiness was observed to increase with age [see Adverse Reactions (6)].

Age does not appear to have a significant effect on lorazepam pharmacokinetics [see Clinical Pharmacology (12.3)].

In general, dose selection for an elderly patient should start at the low end of the dosing range, reflecting the greater frequency of decreased hepatic, renal, or cardiac function, and of concomitant disease or other drug therapy. Greater sensitivity (e.g., sedation) of some older individuals cannot be ruled out [see Warnings and Precautions (5.6)].

8.6 Hepatic Impairment

As with all benzodiazepines, the use of lorazepam, including LOREEV XR, may worsen hepatic encephalopathy. Therefore, LOREEV XR should be used with caution in patients with severe hepatic insufficiency and/or encephalopathy.

9 DRUG ABUSE AND DEPENDENCE

9.1 Controlled Substance

LOREEV XR contains lorazepam, a Schedule IV controlled substance.

9.2 Abuse

LOREEV XR is a benzodiazepine and a CNS depressant with a potential for abuse and addiction. Abuse is the intentional, non-therapeutic use of a drug, even once, for its desirable psychological or physiological effects. Misuse is the intentional use, for therapeutic purposes, of a drug by an individual in a way other than prescribed by a health care provider or for whom it was not prescribed. Drug addiction is a cluster of behavioral, cognitive, and physiological phenomena that may include a strong desire to take the drug, difficulties in controlling drug use (e.g., continuing drug use despite harmful consequences, giving a higher priority to drug use than other activities and obligations), and possible tolerance or physical dependence. Even taking benzodiazepines as prescribed may put patients at risk for abuse and misuse of their medication. Abuse and misuse of benzodiazepines may lead to addiction.

Abuse and misuse of benzodiazepines often (but not always) involve the use of doses greater than the maximum recommended dosage and commonly involve concomitant use of other medications, alcohol, and/or illicit substances, which is associated with an increased frequency of serious adverse outcomes, including respiratory depression, overdose, or death. Benzodiazepines are often sought by individuals who abuse drugs and other substances, and by individuals with addictive disorders [see Warnings and Precautions (5.2)].

The following adverse reactions have occurred with benzodiazepine abuse and/or misuse: abdominal pain, amnesia, anorexia, anxiety, aggression, ataxia, blurred vision, confusion, depression, disinhibition, disorientation, dizziness, euphoria, impaired concentration and memory, indigestion, irritability, muscle pain, slurred speech, tremors, and vertigo.

The following severe adverse reactions have occurred with benzodiazepine abuse and/or misuse: delirium, paranoia, suicidal ideation and behavior, seizures, coma, breathing difficulty, and death. Death is more often associated with polysubstance use (especially benzodiazepines with other CNS depressants such as opioids and alcohol).

9.3 Dependence

Physical Dependence

LOREEV XR may produce physical dependence from continued therapy. Physical dependence is a state that develops as a result of physiological adaptation in response to repeated drug use, manifested by withdrawal signs and symptoms after abrupt discontinuation or a significant dose reduction of a drug. Abrupt discontinuation or rapid dosage reduction of benzodiazepines or administration of flumazenil, a benzodiazepine antagonist, may precipitate acute withdrawal reactions, including seizures, which can be life-threatening. Patients at an increased risk of withdrawal adverse reactions after benzodiazepine discontinuation or rapid dosage reduction include those who take higher dosages (i.e., higher and/or more frequent doses) and those who have had longer durations of use [see Warnings and Precautions (5.3)].

To reduce the risk of withdrawal reactions, use a gradual taper to discontinue LOREEV XR or reduce the dosage [see Dosage and Administration (2.4), Warnings and Precautions (5.3)].

Acute Withdrawal Signs and Symptoms

Acute withdrawal signs and symptoms associated with benzodiazepines have included abnormal involuntary movements, anxiety, blurred vision, depersonalization, depression, derealization, dizziness, fatigue, gastrointestinal adverse reactions (e.g., nausea, vomiting, diarrhea, weight loss, decreased appetite), headache, hyperacusis, hypertension, irritability, insomnia, memory impairment, muscle pain and stiffness, panic attacks, photophobia, restlessness, tachycardia, and tremor. More severe acute withdrawal signs and symptoms, including life-threatening reactions, have included catatonia, convulsions, delirium tremens, depression, hallucinations, mania, psychosis, seizures and suicidality.

Protracted Withdrawal Syndrome

Protracted withdrawal syndrome associated with benzodiazepines is characterized by anxiety, cognitive impairment, depression, insomnia, formication, motor symptoms (e.g., weakness, tremor, muscle twitches), paresthesia, and tinnitus that persists beyond 4 to 6 weeks after initial benzodiazepine withdrawal. Protracted withdrawal symptoms may last weeks to more than 12 months. As a result, there may be difficulty in differentiating withdrawal symptoms from potential reemergence or continuation of symptoms for which the benzodiazepine was being used.

Tolerance

Tolerance to LOREEV XR may develop from continued therapy. Tolerance is a physiological state characterized by a reduced response to a drug after repeated administration (i.e., a higher dose of a drug is required to produce the same effect that was once obtained at a lower dose). Tolerance to the therapeutic effect of LOREEV XR may develop; however, little tolerance develops to the amnestic reactions and other cognitive impairments caused by benzodiazepines.

10 OVERDOSAGE

Overdosage of benzodiazepines is characterized by central nervous system depression ranging from drowsiness to coma. In mild to moderate cases, symptoms can include drowsiness, confusion, dysarthria, lethargy, hypnotic state, diminished reflexes, ataxia, and hypotonia. Rarely, paradoxical or disinhibitory reactions (including agitation, irritability, impulsivity, violent behavior, confusion, restlessness, excitement, and talkativeness) may occur. In severe overdosage cases, patients may develop respiratory depression and coma. Overdosage of benzodiazepines in combination with other CNS depressants (including alcohol and opioids) may be fatal [see Warnings and Precautions (5.2)]. Markedly abnormal (lowered or elevated) blood pressure, heart rate, or respiratory rate raise the concern that additional drugs and/or alcohol are involved in the overdosage.

In managing benzodiazepine overdosage, employ general supportive measures, including intravenous fluids and airway management. Flumazenil, a specific benzodiazepine receptor antagonist indicated for the complete or partial reversal of the sedative effects of benzodiazepines in the management of benzodiazepine overdosage, can lead to withdrawal and adverse reactions, including seizures, particularly in the context of mixed overdosage with drugs that increase seizure risk (e.g., tricyclic and tetracyclic antidepressants) and in patients with long-term benzodiazepine use and physical dependency. The risk of withdrawal seizures with flumazenil use may be increased in patients with epilepsy. Flumazenil is contraindicated in patients who have received a benzodiazepine for control of a potentially lifethreatening condition (e.g., status epilepticus). If the decision is made to use flumazenil, it should be used as an adjunct to, not as a substitute for, supportive management of benzodiazepine overdosage. See the flumazenil injection Prescribing Information.

Consider contacting the Poison Help line (1-800-222-1222) or medical toxicologist for additional overdosage management recommendations.

11 DESCRIPTION

LOREEV XR contains lorazepam, a benzodiazepine. Lorazepam is a nearly white crystalline powder and is practically insoluble in water and slightly soluble in alcohol. It is a 1:1 mixture of (R) and (S) isomers. The chemical name is ±-7-chloro-5-(o-chlorophenyl)-1,3-dihydro-3-hydroxy-2H-1,4-benzodiazepin-2-one and its structural formula is:

Molecular formula: C15H10Cl2N2O2; Molecular weight: 321.16

LOREEV XR is intended for oral administration. Each capsule contains 1 mg, 1.5 mg, 2 mg, or 3 mg of lorazepam. The inactive ingredients are colloidal silicon dioxide, corn starch, gelatin, glyceryl monostearate, hypromellose, lactose monohydrate, methyl acrylate methyl methacrylate and methacrylic acid (7:3:1) copolymer 280000 dispersion, microcrystalline cellulose, polysorbate 80, talc, titanium dioxide, and triethyl citrate. Additionally, the capsule shells contain the following colorants:

1 mg capsules: FD&C Yellow No. 5

1.5 mg capsules: FD&C Blue No. 1 and FD&C Red No. 3

2 mg capsules: D&C Yellow No. 10 and FD&C Red No. 3

3 mg capsules: D&C Yellow No. 10, FD&C Blue No. 1, FD&C Yellow No. 6

12 CLINICAL PHARMACOLOGY

12.1 Mechanism of Action

Lorazepam exerts its effect for the treatment of anxiety disorders through binding to the benzodiazepine site of the gamma-aminobutyric acid-A (GABAA) receptors in the brain and enhances GABA-mediated synaptic inhibition.

12.3 Pharmacokinetics

LOREEV XR pharmacokinetics are dose proportional over the dose range of 1 mg to 3 mg. Steady-state plasma concentrations are typically achieved after 5 days of once-daily administration.

At steady-state, the mean area under concentration curve (AUCTau), the mean peak plasma concentration (Cmax), and the mean minimum plasma concentration (Cmin) of lorazepam following LOREEV XR 3 mg once-daily administration was 694 ng*h/mL, 35 ng/mL and 25 ng/mL, respectively. AUCTau, Cmax, and Cmin of lorazepam from lorazepam tablets following 1 mg, three-times daily administration were 765 ng*h/mL, 41 ng/mL and 29 ng/mL, respectively.

Absorption

Following a single 3 mg dose of LOREEV XR under fasted conditions, the median time to attain Cmax (Tmax) is 14 hours, with a range of 7 to 24 hours.

Effect of Food

Administration of LOREEV XR with a high-fat and high calorie meal did not have a significant effect on exposure of LOREEV XR. However, median Tmax of lorazepam delayed by approximately 2 hours.

LOREEV XR administered under fasted conditions after sprinkling the entire contents onto one-tablespoon (15 mL) of applesauce did not significantly affect exposure and Tmax of lorazepam.

Distribution

Following a single 3 mg dose of LOREEV XR under fasted conditions, the mean apparent volume of distribution is approximately 117 L. At clinically relevant concentrations, lorazepam is approximately 85% bound to plasma proteins.

Elimination

Oral mean plasma clearance (CL/F) is about 72 mL/min in adults following a single 3 mg dose of LOREEV XR and the mean elimination half-life of lorazepam is approximately 20.2 ± 7.2 hours.

Metabolism

Lorazepam is conjugated at its 3-hydroxy group in the liver into lorazepam glucuronide, which has no demonstratable CNS activity in animals.

Excretion

Lorazepam glucuronide is excreted in the urine.

Specific Populations

Geriatric Patients

Studies comparing young and elderly subjects have shown that advancing age does not have a significant effect on the pharmacokinetics of lorazepam tablets. However, a study involving single intravenous doses of 1.5 to 3 mg of lorazepam injection, mean total body clearance of lorazepam decreased by 20% in 15 elderly subjects of 60 to 84 years of age compared to that in 15 younger subjects of 19 to 38 years of age. The clinical significance of the decrease in mean total body clearance of lorazepam injection in geriatric patients is unknown.

Patients with Hepatic Impairment

No pharmacokinetic studies were conducted with LOREEV XR in patients with hepatic impairment.

Patients with Renal Impairment

No pharmacokinetic studies were conducted with LOREEV XR in patients with renal impairment. Lorazepam is poorly dialyzable. Lorazepam glucuronide, the inactive metabolite, may be highly dialyzable.

Drug Interaction Studies

Concurrent administration of lorazepam with valproate, an inhibitor of UGT, results in increased plasma concentrations and reduced clearance of lorazepam [see Dosage and Administration (2.5), Drug Interactions (7)].

Concurrent administration of lorazepam with probenecid, an inhibitor of UGT, may result in a more rapid onset or prolonged effect of lorazepam due to increased half-life and decreased total clearance [see Dosage and Administration (2.5), Drug Interactions (7)].

Alcohol: An in vitro study showed significant increases of lorazepam release from LOREEV XR capsules at 2 hours with approximately 91-95% and 37-42% of the drug release in the presence of 40% and 20% alcohol, respectively [see Drug Interactions (7)]. Effects of 5% and 10% alcohol on drug release were not significant at 2 hours. There is no in vivo study conducted for the effect of alcohol on drug exposure.

13 NONCLINICAL TOXICOLOGY

13.1 Carcinogenesis, Mutagenesis, Impairment of Fertility

Carcinogenesis

No evidence of carcinogenic potential emerged in rats during an 18-month study with lorazepam.

Mutagenesis

No studies regarding mutagenesis have been performed.

Impairment of Fertility

Animal fertility studies have not been conducted with LOREEV XR.

13.2 Animal Toxicology and/or Pharmacology

Esophageal dilation occurred in rats treated with lorazepam for more than one year at 6 mg/kg/day. The no-effect dose was 1.25 mg/kg/day (approximately 1.2 times the maximum recommended human dose of 10 mg/day based on mg/m^2 body surface area). The effect was reversible only when the treatment was withdrawn within two months of first observation of the phenomenon. The clinical significance of this is unknown.

16 HOW SUPPLIED/STORAGE AND HANDLING

LOREEV XR (lorazepam) extended-release capsules are available as:

1 mg: Hard gelatin capsules with an opaque white body, yellow cap and grey printing ink; "ALM" is printed axially on the yellow cap and "658" is printed axially on the opaque white body.
NDC 52427-658-30, bottle of 30 capsules with child-resistant closure
NDC 52427-658-01, bottle of 100 capsules with child-resistant closure

1.5 mg: Hard gelatin capsules with an opaque white body, purple cap and black printing ink; "ALM" is printed axially on the purple cap and "661" is printed axially on the opaque white body.
NDC 52427-661-30, bottle of 30 capsules with child-resistant closure
NDC 52427-661-01, bottle of 100 capsules with child-resistant closure

2 mg: Hard gelatin capsules with an opaque white body, orange cap and grey printing ink; "ALM" is printed axially on the orange cap and "663" is printed axially on the opaque white body.
NDC 52427-663-30, bottle of 30 capsules with child-resistant closure
NDC 52427-663-01, bottle of 100 capsules with child-resistant closure

3 mg: Hard gelatin capsules with an opaque white body, yellowish-green cap and grey printing ink; "ALM" is printed axially on the yellowish-green cap and "667" is printed axially on the opaque white body.
NDC 52427-667-30, bottle of 30 capsules with child-resistant closure
NDC 52427-667-01, bottle of 100 capsules with child-resistant closure

Storage

Store at 20°C to 25°C (68°F to 77°F); excursions permitted to 15°C to 30°C (59°F to 86°F) [see USP Controlled Room Temperature].

Keep bottles tightly closed. Dispense in a tight container.

17 PATIENT COUNSELING INFORMATION

Advise the patient to read the FDA‐approved patient labeling (Medication Guide).

Risks from Concomitant Use with Opioids

Advise patients and caregivers about the risks of potentially fatal respiratory depression and sedation when LOREEV XR is used with opioids and not to use such drugs concomitantly unless supervised by a health care provider. Advise patients not to drive or operate heavy machinery until the effects of concomitant use with the opioid have been determined [see Warnings and Precautions (5.1), Drug Interactions (7)].

Abuse, Misuse, and Addiction

Inform patients that the use of LOREEV XR, even at recommended dosages, exposes users to risks of abuse, misuse, and addiction, which can lead to overdose and death, especially when used in combination with other medications (e.g., opioid analgesics), alcohol, and/or illicit substances. Inform patients about the signs and symptoms of benzodiazepine abuse, misuse, and addiction; to seek medical help if they develop these signs and/or symptoms; and on the proper disposal of unused drug [see Warnings and Precautions (5.2), Drug Abuse and Dependence (9.2)].

Withdrawal Reactions

Inform patients that the continued use of LOREEV XR may lead to clinically significant physical dependence and that abrupt discontinuation or rapid dosage reduction of LOREEV XR may precipitate acute withdrawal reactions, which can be life-threatening. Inform patients that in some cases, patients taking benzodiazepines have developed a protracted withdrawal syndrome with withdrawal symptoms lasting weeks to more than 12 months. Instruct patients that discontinuation or dosage reduction of LOREEV XR may require a slow taper [see Warnings and Precautions (5.3), Drug Abuse and Dependence (9.3)].

CNS Depression

Advise patients about the risks of CNS depression. Instruct patients to avoid the consumption of alcohol during treatment with LOREEV XR. Advise patients to not drive a car or operate heavy machinery until they know how LOREEV XR affects them [see Warnings and Precautions (5.4), Drug Interactions (7)].

Patients with Depression or Psychosis

Advise patients, their families, and caregivers to look for signs of suicidal ideation or worsening depression, and to inform the patient’s healthcare provider immediately [see Warnings and Precautions (5.5)].

Concomitant Medications

Advise patients to inform their healthcare provider of all medicines they take, including prescription and nonprescription medicines, vitamins and herbal supplements [see Drug Interactions (7)].

Administration Information

Advise patients to take LOREEV XR capsules whole or open the capsule and sprinkle the entire contents over a tablespoon of applesauce, followed by drinking water. Advise patients to consume the mixture immediately, without chewing, within 2 hours; do not store for future use [see Dosage and Administration (2.2)].

Pregnancy

Advise pregnant females that use of LOREEV XR late in pregnancy can result in sedation (respiratory depression, lethargy, hypotonia) and/or withdrawal symptoms (hyperreflexia, irritability, restlessness, tremors, inconsolable crying, and feeding difficulties) in newborns [see Warnings and Precautions (5.8), Use in Specific Populations (8.1)]. Instruct patients to inform their healthcare provider if they are pregnant.

Advise pregnant women that there is a pregnancy registry that monitors pregnancy outcomes in women exposed to LOREEV XR [see Use in Specific Populations (8.1)].

Lactation

Advise patients that breastfeeding is not recommended during treatment with LOREEV XR [see Use in Specific Populations (8.2)].

Distributed by:
Almatica Pharma LLC
Morristown, NJ 07960 USA

Loreev XR is protected by U.S. Patent No. 8,999,393.

Loreev XR is a registered trademark of Almatica Pharma LLC.

PI658-02

MEDICATION GUIDE

LOREEV XR (lor-EEV ECKS-AR)

(lorazepam)

extended-release capsules, CIV

What is the most important information I should know about LOREEV XR?

LOREEV XR may cause serious side effects, including:

- LOREEV XR is a benzodiazepine medicine. Taking benzodiazepines with opioid medicines, alcohol, or other central nervous system (CNS) depressants (including street drugs) can cause severe drowsiness, breathing problems (respiratory depression), coma and death. Get emergency help right away if any of the following happens:
  - shallow or slowed breathing
  - breathing stops (which may lead to the heart stopping)
  - excessive sleepiness (sedation)

Do not drive or operate heavy machinery until you know how taking LOREEV XR with opioids affects you.

- Risk of abuse, misuse, and addiction. There is a risk for abuse, misuse, and addiction with benzodiazepines including LOREEV XR which can lead to overdose and serious side effects including coma and death.
  - Serious side effects including coma and death have happened in people who have abused or misused benzodiazepines, including LOREEV XR. These serious side effects may also include delirium, paranoia, suicidal thoughts or actions, seizures, and difficulty breathing. Call your healthcare provider or go to the nearest hospital emergency room right away if you develop any of these serious side effects.
  - You can develop an addiction even if you take LOREEV XR as prescribed by your healthcare provider.
  - Take LOREEV XR exactly as your healthcare provider prescribed.
  - Do not share your LOREEV XR with other people.
  - Keep LOREEV XR in a safe place and away from children.
- Physical dependence and withdrawal reactions. LOREEV XR can cause physical dependence and withdrawal reactions, especially if you continue to take LOREEV XR for several days to several weeks.
  - Do not suddenly stop taking LOREEV XR. Stopping LOREEV XR suddenly can cause serious and life-threatening side effects, including, unusual movements, responses, or expressions, seizures, sudden and severe mental or nervous system changes, depression, seeing or hearing things that others do not see or hear, an extreme increase in activity or talking, losing touch with reality, and suicidal thoughts or actions. Call your healthcare provider or go to the nearest hospital emergency room right away if you develop any of these serious side effects.
  - Some people who stop taking benzodiazepines have symptoms that can last for several weeks to more than 12 months, including, anxiety, trouble remembering, learning, or concentrating, depression, problems sleeping, feeling like insects are crawling under your skin, weakness, shaking, muscle twitching, burning or prickling feeling in your hands, arms, legs or feet, and ringing in your ears.
  - Physical dependence is not the same as drug addiction. Your healthcare provider can tell you more about the differences between physical dependence and drug addiction.
  - Do not take more LOREEV XR than prescribed or take LOREEV XR for longer than prescribed.

What is LOREEV XR?

LOREEV XR is a prescription medicine used to treat anxiety disorders in adults who are receiving stable, evenly divided, 3 times a day dosing with lorazepam tablets.

- LOREEV XR is a federally controlled substance (CIV) because it contains lorazepam that can be abused or lead to dependence. Keep LOREEV XR in a safe place to prevent misuse and abuse. Selling or giving away LOREEV XR may harm others, and is against the law. Tell your healthcare provider if you have abused or been dependent on alcohol, prescription medicines or street drugs.
- It is not known if LOREEV XR is safe or effective in children.
- It is not known if LOREEV XR is safe and effective for use for longer than 4 months.

Do not take LOREEV XR if you:

- are allergic to lorazepam, other benzodiazepines, or any of the ingredients in LOREEV XR. See the end of this Medication Guide for a complete list of ingredients in LOREEV XR.
- have acute narrow angle glaucoma

Before taking LOREEV XR, tell your healthcare provider about all of your medical conditions, including if you:

- have or have had depression, mood problems, or suicidal thoughts or behavior
- have a history of drug or alcohol abuse or addiction
- have lung disease or breathing problems (such as COPD, sleep apnea syndrome)
- have liver or kidney problems
- have or have had seizures
- are pregnant or plan to become pregnant.
  - Taking LOREEV XR late in pregnancy may cause your baby to have symptoms of sedation (breathing problems, sluggishness, low muscle tone), and/or withdrawal symptoms (jitteriness, irritability, restlessness, shaking, excessive crying, feeding problems).
  - Tell your healthcare provider right away if you become pregnant or think you are pregnant during treatment with LOREEV XR.
  - There is a pregnancy registry for women who take LOREEV XR during pregnancy. The purpose of the registry is to collect information about the health of you and your baby. If you become pregnant during treatment with LOREEV XR, talk to your healthcare provider about registering with the National Pregnancy Registry for Psychiatric Medications. You can register by calling 1-866-961-2388 or visiting https://womensmentalhealth.org/pregnancyregistry/.
- are breastfeeding or plan to breastfeed. LOREEV XR passes into your breast milk.
  - Talk to your healthcare provider about the best way to feed your baby if you take LOREEV XR.
  - Breastfeeding is not recommended during treatment with LOREEV XR.

Tell your healthcare provider about all the medicines you take, including prescription and over-the-counter medicines, vitamins, and herbal supplements.

Keep a list of all medicines to show your healthcare provider and pharmacist when you get a new medicine.

LOREEV XR can affect the way other medicines work and other medicines may affect how LOREEV XR works. Taking LOREEV XR with certain other medicines can cause serious side effects.

Do not start or stop other medicines without first talking to your healthcare provider.

How should I take LOREEV XR?

- Take LOREEV XR exactly as your healthcare provider tells you to take it.
- Take LOREEV XR 1 time a day in the morning.
- Take LOREEV XR with or without food.
- Do not crush or chew LOREEV XR capsules.
- Swallow LOREEV XR capsules whole. If you cannot swallow the capsules whole, the capsule may be opened and the entire contents sprinkled onto a tablespoon of applesauce.
  - Swallow all the LOREEV XR mixture without chewing.
  - Swallow the LOREEV XR mixture within 2 hours of mixing. Do not store the mixture for future use.
  - After swallowing the LOREEV XR mixture, follow with a drink of water.
- If you take too much LOREEV XR, call your healthcare provider or poison control center at 1-800-222-1222 or go to the nearest hospital emergency room right away.

What should I avoid while taking LOREEV XR?

- LOREEV XR can cause you to be drowsy. Do not drive a car or operate heavy machinery until you know how LOREEV XR affects you.
- You should not drink alcohol during treatment with LOREEV XR. Drinking alcohol can increase your chances of having serious side effects.

What are the possible side effects of LOREEV XR?

LOREEV XR may cause serious side effects, including:

- See “What is the most important information I should know about LOREEV XR?”
- LOREEV XR can make you sleepy or dizzy, and can slow your thinking and motor skills.
  - Do not drive, operate heavy machinery, or do other dangerous activities until you know how LOREEV XR affects you.
  - Do not drink alcohol or take other drugs that may make you sleepy or dizzy while taking LOREEV XR without first talking to your healthcare provider. When taken with alcohol or drugs that cause sleepiness or dizziness, LOREEV XR may make your sleepiness or dizziness much worse.
- Depression and psychosis. Pre-existing depression may emerge or worsen during use of benzodiazepines including LOREEV XR.
- Abnormal thought and behavior (paradoxical reactions). Symptoms include agitation, irritability, impulsiveness, violent behavior, confusion, restlessness, excitement and talking more than normal.
- Allergic reactions to FD&C Yellow No. 5. LOREEV XR 1 mg capsules contain FD&C Yellow No. 5 (tartrazine), which may cause allergic type reactions in certain people. Symptoms may include bronchial asthma or trouble breathing. Get emergency medical help right away if you have these symptoms after taking LOREEV XR.
- Breathing problems. Slowed breathing and stopping breathing has happened in people who have breathing problems and take benzodiazepines like LOREEV XR.
- Changes in lab tests. Your healthcare provider should do blood tests to check your blood counts and your liver function during treatment if you are on long-term treatment with LOREEV XR.

The most common side effects of LOREEV XR include sedation, dizziness, weakness, unsteadiness.

These are not all the possible side effects of LOREEV XR.

Call your doctor for medical advice about side effects. You may report side effects to FDA at 1-800-FDA-1088.

How should I store LOREEV XR?

- Store LOREEV XR in a tightly closed container at room temperature between 68°F to 77°F (20°C to 25°C).
- Keep LOREEV XR and all medicines out of the reach of children.

General information about the safe and effective use of LOREEV XR.
Medicines are sometimes prescribed for purposes other than those listed in a Medication Guide. Do not use LOREEV XR for a condition for which it was not prescribed. Do not give LOREEV XR to other people, even if they have the same symptoms that you have. It may harm them. You can ask your pharmacist or healthcare provider for information about LOREEV XR that is written for health professionals.

What are the ingredients in LOREEV XR?

Active ingredient: lorazepam

Inactive ingredients: colloidal silicon dioxide, corn starch, gelatin, glyceryl monostearate, hypromellose, lactose monohydrate, methyl acrylate methyl methacrylate and methacrylic acid (7:3:1) copolymer 280000 dispersion, microcrystalline cellulose, polysorbate 80, talc, titanium dioxide, and triethyl citrate. Additionally, the capsule shells contain the following colorants:

1 mg capsules: FD&C Yellow No. 5
1.5 mg capsules: FD&C Blue No. 1 and FD&C Red No. 3

2 mg capsules: D&C Yellow No. 10 and FD&C Red No. 3

3 mg capsules: D&C Yellow No. 10, FD&C Blue No. 1, FD&C Yellow No. 6

Distributed by:
Almatica Pharma LLC
Morristown, NJ 07960 USA

Loreev XR is protected by U.S. Patent No. 8,999,393. Loreev XR is a registered trademark of Almatica Pharma LLC.

For more information, visit www.loreevxr.com or call 1-877-447-7979.

This Medication Guide has been approved by the U.S. Food and Drug Administration.

Revised: 01/2023

PL658-02

PACKAGE LABEL PRINCIPAL DISPLAY PANEL SECTION

NDC 52427-658-30

Loreev XR® CIV
(lorazepam) Extended-Release Capsules

1 mg

PHARMACIST: Dispense the accompanying Medication Guide to each patient.

Contains FD&C Yellow No. 5 (tartrazine) as a color additive.

PACKAGE LABEL PRINCIPAL DISPLAY PANEL SECTION

NDC 52427-661-30

Loreev XR® CIV
(lorazepam) Extended-Release Capsules

1.5 mg

PHARMACIST: Dispense the accompanying Medication Guide to each patient.

PACKAGE LABEL PRINCIPAL DISPLAY PANEL SECTION

NDC 52427-663-30

Loreev XR® CIV
(lorazepam) Extended-Release Capsules

2 mg

PHARMACIST: Dispense the accompanying Medication Guide to each patient.

PACKAGE LABEL PRINCIPAL DISPLAY PANEL SECTION

NDC 52427-667-30

Loreev XR® CIV
(lorazepam) Extended-Release Capsules

3 mg

PHARMACIST: Dispense the accompanying Medication Guide to each patient.

Contains FD&C Yellow No. 6